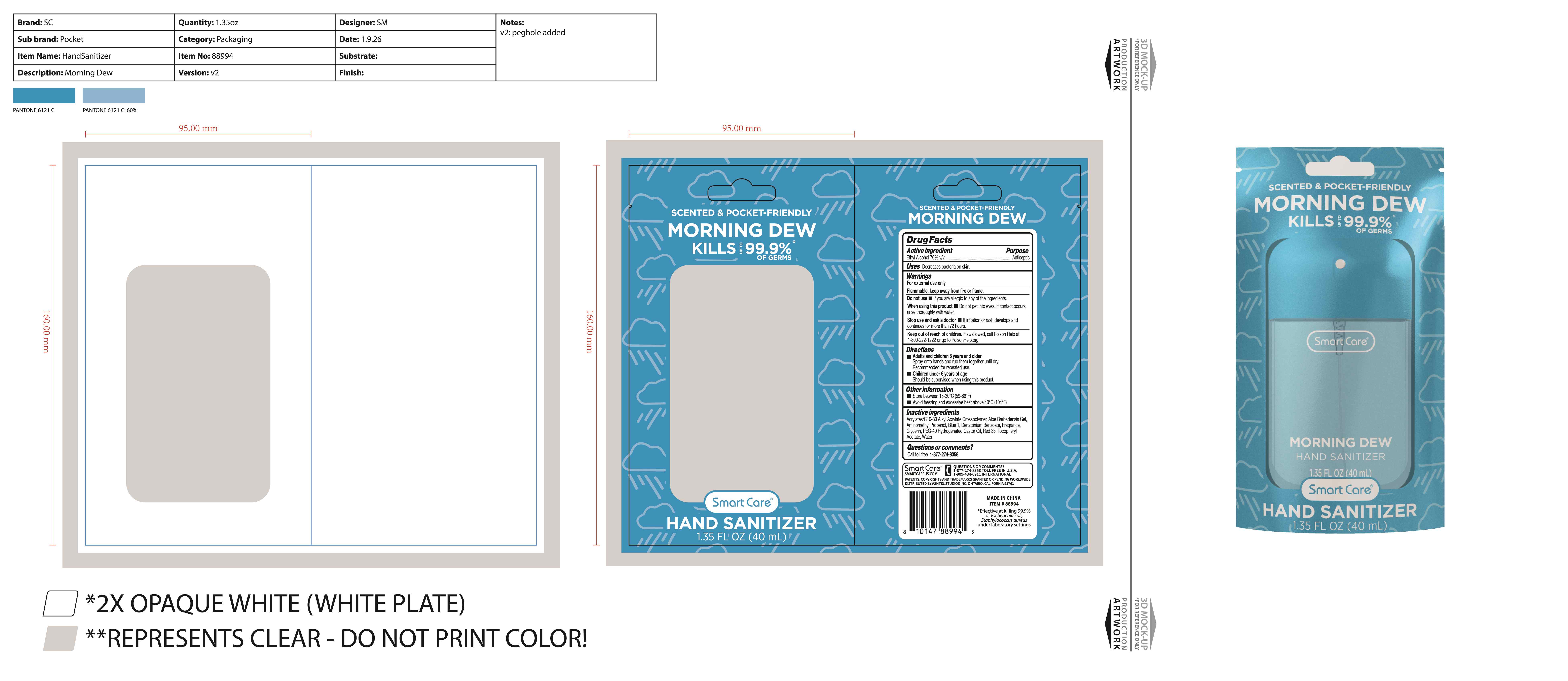 DRUG LABEL: Smart Care Hand Sanitizer Morning Dew
NDC: 54860-555 | Form: SPRAY
Manufacturer: Shenzhen Lantern Scicence Co.,Ltd.
Category: otc | Type: HUMAN OTC DRUG LABEL
Date: 20260203

ACTIVE INGREDIENTS: ALCOHOL 70 mL/100 mL
INACTIVE INGREDIENTS: GLYCERIN; ACRYLATES/C10-30 ALKYL ACRYLATE CROSSPOLYMER (60000 MPA.S); .ALPHA.-TOCOPHEROL ACETATE; DENATONIUM BENZOATE; AMINOMETHYLPROPANOL; ALOE VERA LEAF; FD&C BLUE NO. 1; D&C RED NO. 33; PEG-40 HYDROGENATED CASTOR OIL; WATER

Smart Care Hand Sanitizer Morning Dew

Active Ingredient

Active ingredient Purpose

Ethyl Alcohol 70% v/v Antiseptic

Uses

Decreases bacieria on skin

Warning

For external use only

Do not use

lf you are allergic to any of the ingredients

When using this product

Do not get into eyes. lf contact occurs, rinse thoroughly with water.Do not use in or near eyes,In case of eye contact ,flush eyes thoroughly with water. Discontinue if skin becomes irritated and ask for a doctor.

Stop use and ask a doctor

lf irritation or rash develops and continues for more than72 hours.

keep out of reach of children

lf swallowed, get medical help or contact a Poison Control Center immediately.

Directions

Adults and children 6 years and older
Spray onto hands and rub together unil dry. Recommended for repeat use.
Children under 6 years of age
should be supervised when using this product.

Inactive ingredients

Acrylates/C10-30 Alkyl Acrylate Crosspolymer, Aloe Barbadensis Gel, Aminomethy Propanol, Blue 1, Denatonium Benzoate, Fragrance, Glycerin, PEG-40 Hydrogenated Castor Oil, Red 33, Tocopheryl Acetate, Water.

other Information

Storebetween15-30C(59-86F)
Avoid freezing and excessive heat above 40C (104F)

Questions or comments?

Call toll free 1-877-274-8358

packaging

Packagin